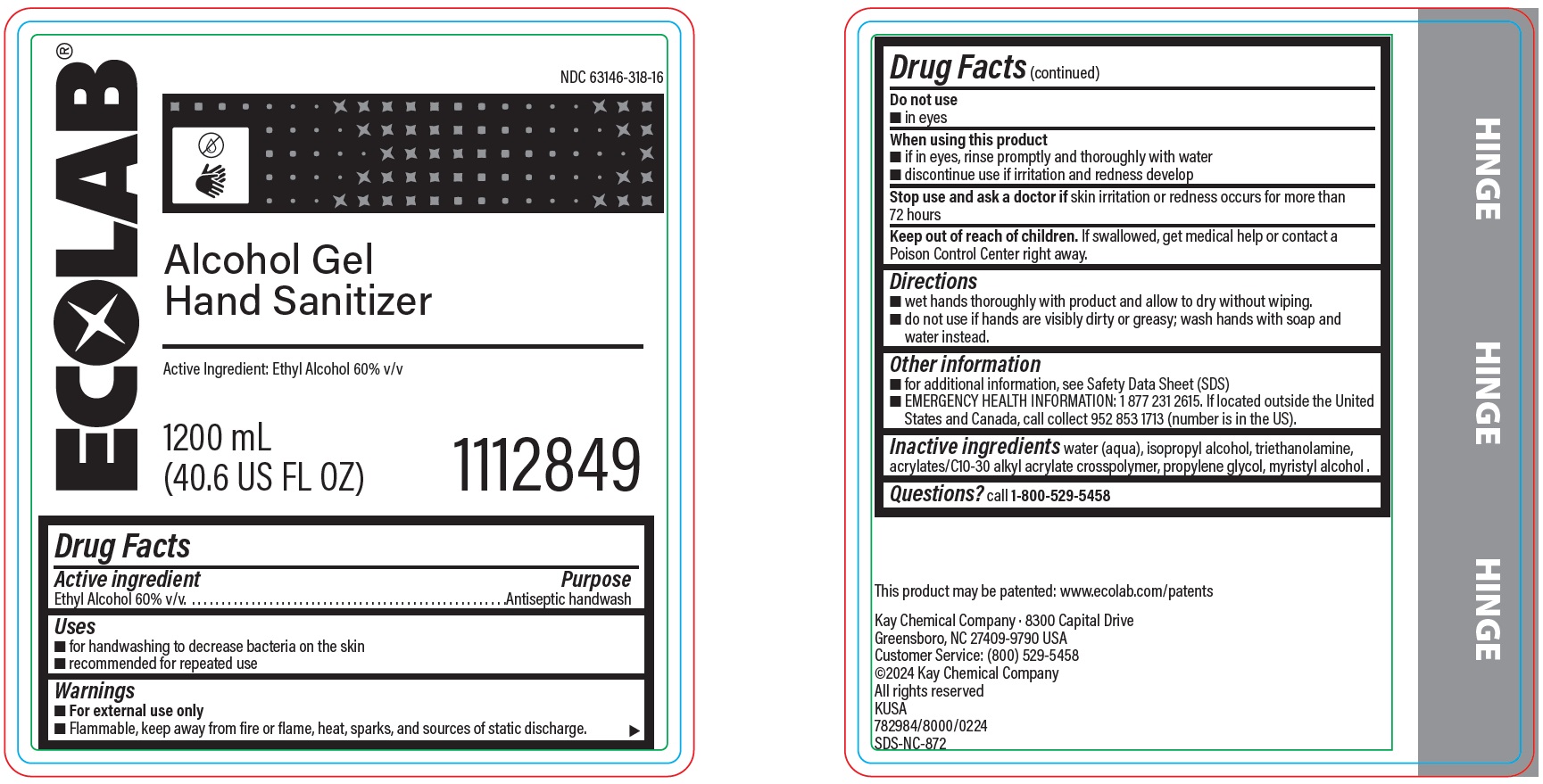 DRUG LABEL: Alcohol Gel Hand Sanitizer
NDC: 47593-690 | Form: SOLUTION
Manufacturer: Ecolab Inc.
Category: otc | Type: HUMAN OTC DRUG LABEL
Date: 20251230

ACTIVE INGREDIENTS: ALCOHOL 60 mL/100 mL
INACTIVE INGREDIENTS: WATER; ISOPROPYL ALCOHOL; TROLAMINE; CARBOMER COPOLYMER TYPE B (ALLYL PENTAERYTHRITOL CROSSLINKED); PROPYLENE GLYCOL; MYRISTYL ALCOHOL

Drug Facts

Active ingredient

Ethyl Alcohol 60% v/v

Purpose

Antiseptic handwash

Uses

- For handwashing to decrease bacteria on skin
- recommended for repeated use

Warnings

- For external use only
- Flammable, keep away from fire or flame, heat, sparks and sources of static discharge.

Do not use

- In eyes

When using this product

- If in eyes, rinse promptly and thoroughly with water
- Discontinue use if irritation and redness develop

Stop use and ask a doctor if

- skin irritation or redness occurs for more than 72 hours

Keep out of reach of children. If swallowed, get medical help or contact a Poison Control Center right away.

Directions

- wet hands thoroughly with product and allow to dry without wiping.
- do not use if hands are visibly dirty or greasy; wash hands with soap and water instead.

Other information

- For additional information, see Safety Data Sheet (SDS)
- EMERGENCY HEALTH INFORMATION: 1 877 231 2615. If located outside the United States and Canada, call collect 952 853 1713 (number is in the US).

Inactive ingredients

water (aqua), isopropyl alcohol, triethanolamine, acrylates/C10-30 alkyl acrylate crosspolymer, propylene glycol, myristyl alcohol

Questions? Call 1-800-529-5458

Principal display panel and representative label

ECOLAB

Alcohol Gel Hand Sanitizer

Active Ingredient: Ethyl Alcohol 60% v/v

1200 mL (40.6 US FL OZ)

1112849

Kay Chemical Company · 8300 Capital Drive

Greensboro, NC 27409-9790 USA

Customer Service: (800) 529-5458

©2024 Kay Chemical Company

All rights reserved

KUSA

782984/8000/0224

SDS-NC-872